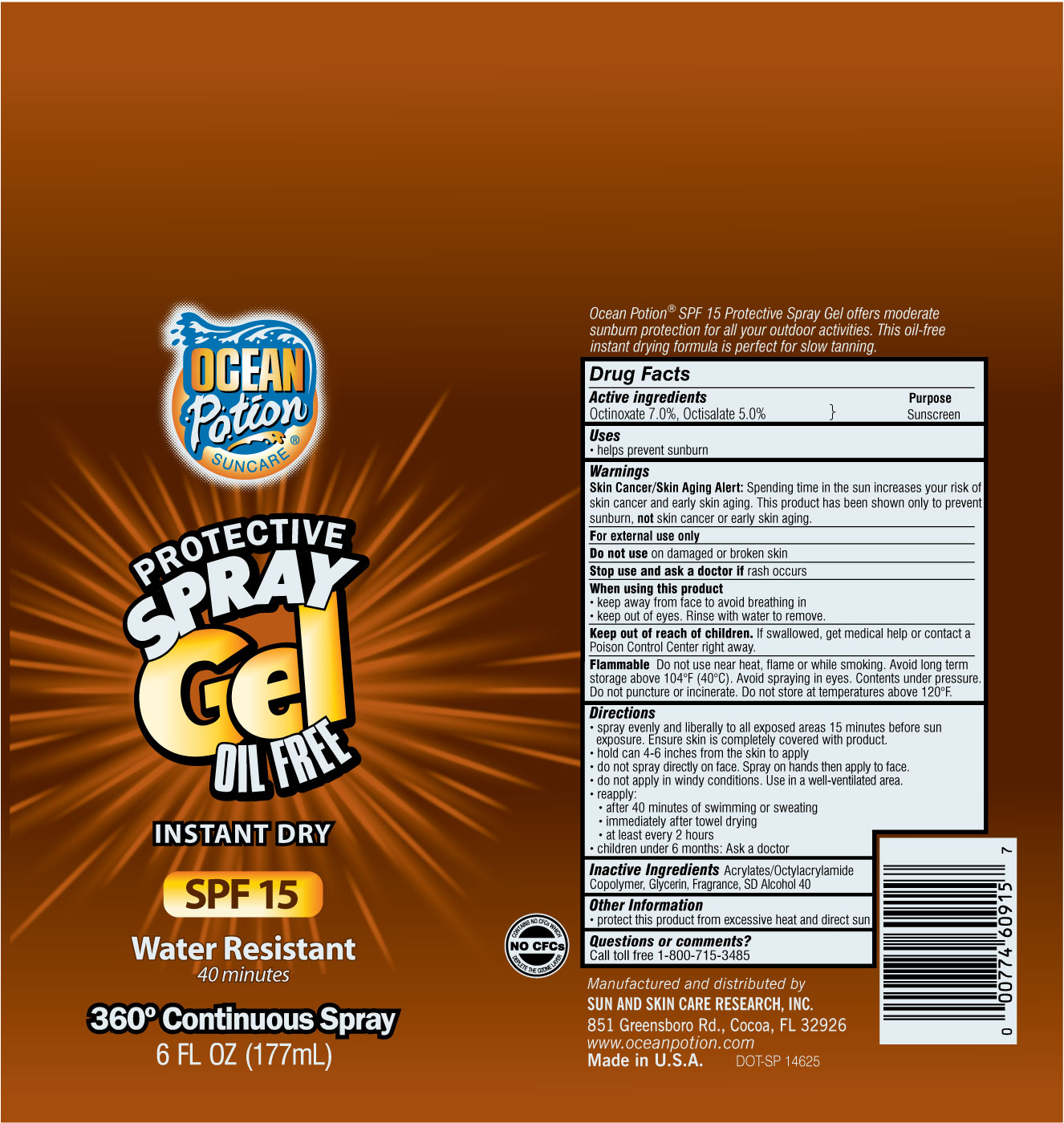 DRUG LABEL: OP Protective Mist 15 Oil Free
NDC: 62802-915 | Form: SPRAY
Manufacturer: Sun & Skin Care Research, LLC
Category: otc | Type: HUMAN OTC DRUG LABEL
Date: 20120518

ACTIVE INGREDIENTS: OCTINOXATE 7.0 mL/100 mL; OCTISALATE 5.0 mL/100 mL
INACTIVE INGREDIENTS: ALCOHOL; GLYCERIN

DRUG FACTS

Active Ingredients

Octinoxate 7.0%
Octisalate 5.0%

Purpose

Sunscreen

Uses

- Helps prevent sunburn

Warnings

Skin Cancer / Skin Aging Alert: Spending time in the sun increases your risk of skin cancer and early skin aging. This product has been shown only to prevent sunburn, not skin cancer or early skin aging.

For external use only. Do not use on damaged or broken skin. Stop use and ask a doctor if rash occurs. When using this product keep away from face to avoid breathing in. Keep out of eyes. Rinse with water to remove. Keep out of the reach of children. If swallowed, get medical help or call a poison control center right away. Flammable Do not use near heat, flame or while smoking. Avoid long term storage above 104° F (40° C). Avoid spraying in eyes. Contents under pressure. Do not puncture or incinerate. Do not store at temperatures above 120° F.

Directions

- spray evenly and liberally to all exposed areas 15 minutes before sun exposure. Ensure skin is completely covered with product.
- hold can 4 - 6 inches away from the skin to apply
- do not spray directly on face. Spray on hands then apply to face.
- do not apply in windy conditions. Use in a well ventilated area.
- reapply after 40 minutes of swimming or sweating, immediately after towel drying and at least every 2 hours
- children under 6 months: Ask a doctor

Other Information

- protect this product from excessive heat and direct sun